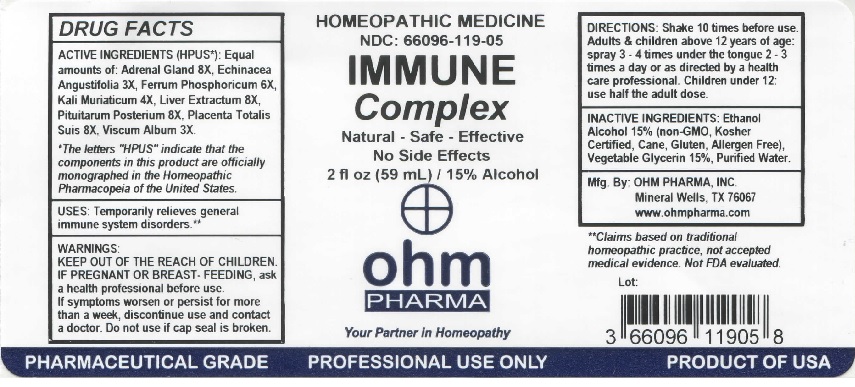 DRUG LABEL: OHM Immune Complex
NDC: 66096-119 | Form: LIQUID
Manufacturer: OHM PHARMA INC.
Category: homeopathic | Type: HUMAN OTC DRUG LABEL
Date: 20211229

ACTIVE INGREDIENTS: BOS TAURUS ADRENAL GLAND 8 [hp_X]/59 mL; ECHINACEA ANGUSTIFOLIA 3 [hp_X]/59 mL; FERROSOFERRIC PHOSPHATE 6 [hp_X]/59 mL; POTASSIUM CHLORIDE 4 [hp_X]/59 mL; MAMMAL LIVER 8 [hp_X]/59 mL; SUS SCROFA PITUITARY GLAND, POSTERIOR 8 [hp_X]/59 mL; SUS SCROFA PLACENTA 8 [hp_X]/59 mL; VISCUM ALBUM FRUITING TOP 3 [hp_X]/59 mL
INACTIVE INGREDIENTS: ALCOHOL; GLYCERIN; WATER

OHM Immune Complex

ACTIVE INGREDIENT

ACTIVE INGREDIENTS (HPUS*): Equal amounts of: Adrenal Gland 8X, Echinacea Angustifolia 3X, Ferrum Phosphoricum 6X, Kali Muriaticum 4X, Liver Extractum 8X, Pituitarum Posterium 8X, Placenta Totalis Suis 8X, Viscum Album 3X.

*The letters "HPUS" indicate that the components in this product are officially monographed in the Homeopathic Pharmacopeia of the United States.

INDICATIONS AND USAGE

Uses: Temporarily relieves general immune system disorders.**

**Claims based on traditional homeopathic practice, not accepted medical evidence. Not FDA evaluated.

WARNINGS

WARNINGS: IF PREGNANT OR BREAST-FEEDING, ask a health professional before use. If symptoms worsen or persist for more than a week, discontinue use and contact a doctor.

- KEEP OUT OF REACH OF CHILDREN.

DOSAGE AND ADMINISTRATION

DIRECTIONS: Shake 10 times before use. Adults & children above 12 years of age: spray 3-4 times under the tongue 2-3 times a day or as directed by a health care professional. Children under 12: use half the adult dose.

Do not use if cap seal is broken.

INACTIVE INGREDIENT

INACTIVE INGREDIENTS: Ethanol Alcohol 15% (non-GMO, Kosher Certified, Cane, Gluten, Allergen Free), Vegetable Glycerin 15%, Purified Water.

QUESTIONS

Mfg. By: OHM PHARMA, INC. Mineral Wells, TX 76067

www.ohmpharma.com

PACKAGE LABEL

HOMEOPATHIC MEDICINE

NDC: 66096-119-05

IMMUNE Complex

Natural - Safe - Effective

No Side Effects

2 fl oz (59mL) / Alcohol

PRODUCT OF USA

PURPOSE

Temporarily relieves general immune system disorders.